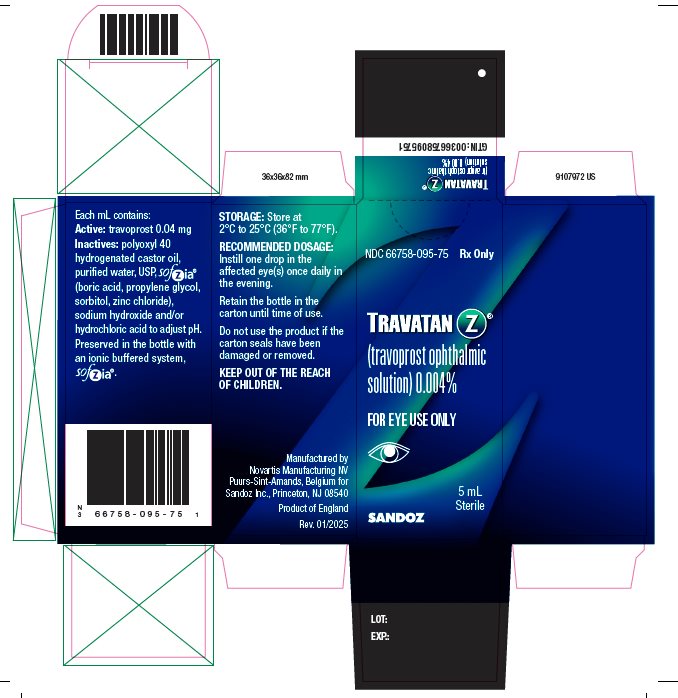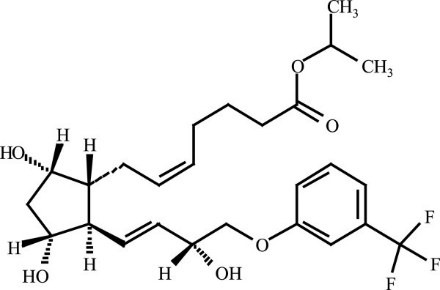 DRUG LABEL: Travatan Z
NDC: 66758-095 | Form: SOLUTION/ DROPS
Manufacturer: Sandoz Inc
Category: prescription | Type: HUMAN PRESCRIPTION DRUG LABEL
Date: 20250131

ACTIVE INGREDIENTS: TRAVOPROST 0.04 mg/1 mL
INACTIVE INGREDIENTS: POLYOXYL 40 HYDROGENATED CASTOR OIL; BORIC ACID; PROPYLENE GLYCOL; SORBITOL; ZINC CHLORIDE; SODIUM HYDROXIDE; HYDROCHLORIC ACID; WATER

HIGHLIGHTS OF PRESCRIBING INFORMATION

These highlights do not include all the information needed to use TRAVATAN Z safely and effectively. See full prescribing information for TRAVATAN Z.
TRAVATAN Z® (travoprost ophthalmic solution), for topical ophthalmic use
Initial U.S. Approval: 2001

1 INDICATIONS AND USAGE

TRAVATAN Z is a prostaglandin analog indicated for the reduction of elevated intraocular pressure (IOP) in patients with open-angle glaucoma or ocular hypertension (1)

2 DOSAGE AND ADMINISTRATION

One drop in the affected eye(s) once daily in the evening (2)

3 DOSAGE FORMS AND STRENGTHS

Ophthalmic solution containing travoprost 0.04 mg/mL (3)

4 CONTRAINDICATIONS

None (4)

5 WARNINGS AND PRECAUTIONS

- Pigmentation: Pigmentation of the iris, periorbital tissue (eyelid), and eyelashes can occur. Iris pigmentation likely to be permanent (5.1)
- Eyelash Changes: Gradual change to eyelashes including increased length, thickness and number of lashes. Usually reversible (5.2)

6 ADVERSE REACTIONS

Most common adverse reaction (30% to 50%) is conjunctival hyperemia (6.1)

To report SUSPECTED ADVERSE REACTIONS, contact Sandoz Inc. at 1-800-525-8747 or FDA at 1-800-FDA-1088 or www.fda.gov/medwatch.

8 USE IN SPECIFIC POPULATIONS

Use in pediatric patients below the age of 16 years is not recommended because of potential safety concerns related to increased pigmentation following long-term chronic use (8.4)

FULL PRESCRIBING INFORMATION

1 INDICATIONS AND USAGE

TRAVATAN Z® (travoprost ophthalmic solution) 0.004% is indicated for the reduction of elevated intraocular pressure (IOP) in patients with open-angle glaucoma or ocular hypertension.

2 DOSAGE AND ADMINISTRATION

The recommended dosage is one drop in the affected eye(s) once daily in the evening. TRAVATAN Z should not be administered more than once daily since it has been shown that more frequent administration of prostaglandin analogs may decrease the IOP-lowering effect.

Reduction of the IOP starts approximately 2 hours after the first administration with maximum effect reached after 12 hours.

TRAVATAN Z may be used concomitantly with other topical ophthalmic drug products to lower IOP. If more than one topical ophthalmic drug is being used, the drugs should be administered at least 5 minutes apart.

3 DOSAGE FORMS AND STRENGTHS

Ophthalmic solution containing travoprost 0.04 mg/mL.

4 CONTRAINDICATIONS

None.

5 WARNINGS AND PRECAUTIONS

5.1 Pigmentation

Travoprost ophthalmic solution has been reported to cause changes to pigmented tissues. The most frequently reported changes have been increased pigmentation of the iris, periorbital tissue (eyelid), and eyelashes. Pigmentation is expected to increase as long as travoprost is administered. The pigmentation change is due to increased melanin content in the melanocytes rather than to an increase in the number of melanocytes. After discontinuation of travoprost, pigmentation of the iris is likely to be permanent, while pigmentation of the periorbital tissue and eyelash changes have been reported to be reversible in some patients. Patients who receive treatment should be informed of the possibility of increased pigmentation. The long-term effects of increased pigmentation are not known.

Iris color change may not be noticeable for several months to years. Typically, the brown pigmentation around the pupil spreads concentrically towards the periphery of the iris and the entire iris or parts of the iris become more brownish. Neither nevi nor freckles of the iris appear to be affected by treatment. While treatment with TRAVATAN Z can be continued in patients who develop noticeably increased iris pigmentation, these patients should be examined regularly.

5.2 Eyelash Changes

TRAVATAN Z may gradually change eyelashes and vellus hair in the treated eye. These changes include increased length, thickness, and number of lashes. Eyelash changes are usually reversible upon discontinuation of treatment.

5.3 Intraocular Inflammation

TRAVATAN Z should be used with caution in patients with active intraocular inflammation (e.g., uveitis) because the inflammation may be exacerbated.

5.4 Macular Edema

Macular edema, including cystoid macular edema, has been reported during treatment with travoprost ophthalmic solution. TRAVATAN Z should be used with caution in aphakic patients, in pseudophakic patients with a torn posterior lens capsule, or in patients with known risk factors for macular edema.

5.5 Angle-closure, Inflammatory or Neovascular Glaucoma

TRAVATAN Z has not been evaluated for the treatment of angle-closure, inflammatory or neovascular glaucoma.

5.6 Bacterial Keratitis

There have been reports of bacterial keratitis associated with the use of multiple-dose containers of topical ophthalmic products. These containers had been inadvertently contaminated by patients who, in most cases, had a concurrent corneal disease or a disruption of the ocular epithelial surface.

5.7 Use with Contact Lenses

Contact lenses should be removed prior to instillation of TRAVATAN Z and may be reinserted 15 minutes following its administration.

6 ADVERSE REACTIONS

6.1 Clinical Trials Experience

Because clinical trials are conducted under widely varying conditions, adverse reaction rates observed in the clinical trials of a drug cannot be directly compared to rates in the clinical trials of another drug and may not reflect the rates observed in practice.

The most common adverse reaction observed in controlled clinical trials with TRAVATAN and TRAVATAN Z was ocular hyperemia, which was reported in 30% to 50% of patients. Up to 3% of patients discontinued therapy due to conjunctival hyperemia. Ocular adverse reactions, reported at an incidence of 5% to 10% in these clinical trials, included decreased visual acuity, eye discomfort, foreign body sensation, pain, and pruritus.

Ocular adverse reactions, reported at an incidence of 1% to 4% in clinical trials with TRAVATAN or TRAVATAN Z, included abnormal vision, blepharitis, blurred vision, cataract, conjunctivitis, corneal staining, dry eye, iris discoloration, keratitis, lid margin crusting, ocular inflammation, photophobia, subconjunctival hemorrhage, and tearing.

Non-ocular adverse reactions, reported at an incidence of 1% to 5% in these clinical studies, were allergy, angina pectoris, anxiety, arthritis, back pain, bradycardia, bronchitis, chest pain, cold/flu syndrome, depression, dyspepsia, gastrointestinal disorder, headache, hypercholesterolemia, hypertension, hypotension, infection, pain, prostate disorder, sinusitis, urinary incontinence, and urinary tract infections.

6.2 Postmarketing Experience

Additional adverse reactions have been identified during postapproval use of TRAVATAN or TRAVATAN Z in clinical practice. Because they are reported voluntarily from a population of unknown size, estimates of frequency cannot be made. The reactions, which have been chosen for inclusion due to either their seriousness, frequency of reporting, possible causal connection to TRAVATAN or TRAVATAN Z, or a combination of these factors, include: arrhythmia, vomiting, epistaxis, tachycardia, and insomnia.

In postmarketing use with prostaglandin analogs, periorbital and lid changes, including deepening of the eyelid sulcus have been observed.

8 USE IN SPECIFIC POPULATIONS

8.1 Pregnancy

Risk Summary

There are no adequate and well-controlled studies in pregnant women to inform a drug-associated risk.

In animal reproduction studies, subcutaneous (SC) administration of travoprost to pregnant mice and rats throughout the period of organogenesis produced embryo-fetal lethality, spontaneous abortion, and premature delivery at potentially clinically relevant doses.

Advise pregnant women of a potential risk to a fetus. Because animal reproductive studies are not always predictive of human response, TRAVATAN Z should be administered during pregnancy only if the potential benefit justifies the potential risk to the fetus.

The background risk of major birth defects and miscarriage for the indicated population is unknown; however, in the U.S. general population, the estimated background risk of major birth defects is 2% to 4% and of miscarriage is 15% to 20% of clinically recognized pregnancies.

Data

Animal Data

An embryo-fetal study was conducted in pregnant rats administered travoprost once daily by SC injection from gestation day (GD) 6 to 18, to target the period of organogenesis. At 10 mcg/kg (60 times the maximum recommended human ocular dose [MRHOD], based on estimated plasma Cmax), travoprost was teratogenic in rats, evidenced by an increase in the incidence of skeletal malformations as well as external and visceral malformations, including fused sternebrae, domed head and hydrocephaly. Travoprost caused post-implantation loss at 10 mcg/kg. The no observed adverse effect level (NOAEL) for post-implantation loss was 3 mcg/kg (18 times the MRHOD, based on estimated plasma Cmax). The maternal NOAEL was 10 mcg/kg.

An embryo-fetal study was conducted in pregnant mice administered travoprost once daily by SC injection from GD 6 to 11, to target the period of organogenesis. At 1 mcg/kg (6 times the MRHOD, based on estimated plasma Cmax), travoprost caused postimplantation loss and decreased fetal weight. The NOAEL for malformations was 0.3 mcg/kg (2 times the MRHOD, based on estimated plasma Cmax). The maternal NOAEL was 1 mcg/kg.

Pre/postnatal studies were conducted in rats administered travoprost once daily by subcutaneous injection from GD 7 (early embryonic period) to postnatal Day 21 (end of lactation period). At doses of greater than or equal to 0.12 mcg/kg/day (0.7 times the MRHOD, based on estimated plasma Cmax), adverse pregnancy outcomes (embryo-fetal lethality, abortion, and early delivery), low-birth weight and developmental delays were observed. The NOAEL for adverse pregnancy outcomes, low-birth weight and developmental delay was 0.1 mcg/kg (0.6 times the MRHOD, based on estimated plasma Cmax). The NOAEL for maternal toxicity was 0.72 mcg/kg (4 times the MRHOD, based on estimated plasma Cmax).

8.2 Lactation

Risk Summary

There are no data on the effects of travoprost on the breastfed child or milk production. It is not known if travoprost is present in human milk following ophthalmic administration. A study in lactating rats demonstrated that radio-labeled travoprost and/or its metabolites were excreted in milk following subcutaneous administration.

The developmental and health benefits of breastfeeding should be considered along with the mother’s clinical need for TRAVATAN Z and any potential adverse effects on the breast-fed child from TRAVATAN Z.

8.4 Pediatric Use

Use in pediatric patients below the age of 16 years is not recommended because of potential safety concerns related to increased pigmentation following long-term chronic use.

8.5 Geriatric Use

No overall clinical differences in safety or effectiveness have been observed between elderly and other adult patients.

8.6 Hepatic and Renal Impairment

Travoprost ophthalmic solution 0.004% has been studied in patients with hepatic impairment and also in patients with renal impairment. No clinically relevant changes in hematology, blood chemistry, or urinalysis laboratory data were observed in these patients.

11 DESCRIPTION

Travoprost is a synthetic prostaglandin F analog. Its chemical name is [1R-[1α(Z),2β(1E,3R*),3α,5α]]-7-[3,5-Dihydroxy-2-[3-hydroxy-4-[3-(trifluoromethyl) phenoxy]-1-butenyl]cyclopentyl]-5-heptenoic acid, 1-methylethylester. It has a molecular formula of C26H35F3O6 and a molecular weight of 500.55 g/mol. The chemical structure of travoprost is:

Travoprost is a clear, colorless to slightly yellow oil that is very soluble in acetonitrile, methanol, octanol, and chloroform. It is practically insoluble in water.

TRAVATAN Z is supplied as sterile, buffered aqueous solution of travoprost with a pH of approximately 5.7 and an osmolality of approximately 290 mOsmol/kg.

TRAVATAN Z contains Active: travoprost 0.04 mg/mL; Inactives: polyoxyl 40 hydrogenated castor oil, purified water, USP, sofZia® (boric acid, propylene glycol, sorbitol, zinc chloride), sodium hydroxide and/or hydrochloric acid to adjust pH. Preserved in the bottle with an ionic buffered system, sofZia®.

12 CLINICAL PHARMACOLOGY

12.1 Mechanism of Action

Travoprost free acid, a prostaglandin analog is a selective FP prostanoid receptor agonist, which is believed to reduce IOP by increasing uveoscleral outflow. The exact mechanism of action is unknown at this time.

12.3 Pharmacokinetics

Travoprost is absorbed through the cornea and is hydrolyzed to the active free acid. Data from 4 multiple-dose pharmacokinetic studies (totaling 107 subjects) have shown that plasma concentrations of the free acid are below 0.01 ng/mL (the quantitation limit of the assay) in two-thirds of the subjects. In those individuals with quantifiable plasma concentrations (N = 38), the mean plasma Cmax was 0.018 ± 0.007 ng/mL (ranged 0.01 to 0.052 ng/mL) and was reached within 30 minutes. From these studies, travoprost is estimated to have a plasma half-life of 45 minutes. There was no difference in plasma concentrations between Days 1 and 7, indicating steady-state was reached early and that there was no significant accumulation.

Travoprost, an isopropyl ester prodrug, is hydrolyzed by esterases in the cornea to its biologically active free acid. Systemically, travoprost free acid is metabolized to inactive metabolites via beta-oxidation of the α (carboxylic acid) chain to give the 1,2-dinor and 1,2,3,4-tetranor analogs, via oxidation of the 15-hydroxyl moiety, as well as via reduction of the 13, 14 double bond.

The elimination of travoprost free acid from plasma was rapid and levels were generally below the limit of quantification within one hour after dosing. The terminal elimination half-life of travoprost free acid was estimated from 14 subjects and ranged from 17 minutes to 86 minutes with the mean half-life of 45 minutes. Less than 2% of the topical ocular dose of travoprost was excreted in the urine within 4 hours as the travoprost free acid.

13 NONCLINICAL TOXICOLOGY

13.1 Carcinogenesis, Mutagenesis, Impairment of Fertility

Two-year carcinogenicity studies in mice and rats at subcutaneous doses of 10, 30, or 100 mcg/kg/day did not show any evidence of carcinogenic potential. However, at 100 mcg/kg/day, male rats were only treated for 82 weeks, and the maximum tolerated dose (MTD) was not reached in the mouse study. The high dose (100 mcg/kg) corresponds to exposure levels 326 times (mouse) and 547 times (rat) the human exposure at the MRHOD of 0.04 mcg/kg, based on estimated plasma Cmax for active travoprost free acid.

Travoprost was not mutagenic in the Ames test, mouse micronucleus test or rat chromosome aberration assay. A slight increase in the mutant frequency was observed in one of two mouse lymphoma assays in the presence of rat S-9 activation enzymes.

Travoprost did not affect mating or fertility indices in male or female rats at subcutaneous doses up to 3 mcg/kg/day (18 times the MRHOD based on estimated plasma Cmax). At 10 mcg/kg/day (60 times the MRHOD, based on estimated plasma Cmax), the mean number of corpora lutea was reduced, and the post-implantation losses were increased.

14 CLINICAL STUDIES

In clinical studies, patients with open-angle glaucoma or ocular hypertension and baseline pressure of 25 to 27 mmHg, who were treated with TRAVATAN or TRAVATAN Z dosed once daily in the evening, demonstrated 7 to 8 mmHg reductions in IOP. In sub-group analyses of these studies, mean IOP reduction in black patients was up to 1.8 mmHg greater than in non-black patients. It is not known at this time whether this difference is attributed to race or to heavily pigmented irides.

In a multi-center, randomized, controlled trial, patients with mean baseline IOP of 24 to 26 mmHg on TIMOPTIC** 0.5% twice daily who were treated with TRAVATAN dosed daily adjunctively to TIMOPTIC** 0.5% twice daily demonstrated 6 to 7 mmHg reductions in IOP.

16 HOW SUPPLIED/STORAGE AND HANDLING

TRAVATAN Z is a sterile, isotonic, buffered, preserved, aqueous solution of travoprost (0.04 mg/mL).

TRAVATAN Z is supplied as a 2.5 mL solution in a 4 mL and a 5 mL solution in a 7.5 mL oval natural polypropylene dispenser bottle with a natural polypropylene dropper tip and a turquoise polypropylene or high-density polyethylene overcap.

2.5 mL fill…………………NDC 66758-095-56

5 mL fill……………………NDC 66758-095-75

Storage: Store at 2°C to 25°C (36°F to 77°F).

After opening, TRAVATAN Z can be used until the expiration date on the bottle.

17 PATIENT COUNSELING INFORMATION

Potential for Pigmentation

Advise the patient about the potential for increased brown pigmentation of the iris, which may be permanent. Inform the patient about the possibility of eyelid skin darkening, which may be reversible after discontinuation of TRAVATAN Z [see Warnings and Precautions (5.1)].

Potential for Eyelash Changes

Inform the patient about the possibility of eyelash and vellus hair changes in the treated eye during treatment with TRAVATAN Z. These changes may result in a disparity between eyes in length, thickness, pigmentation, number of eyelashes or vellus hairs, and/or direction of eyelash growth. Eyelash changes are usually reversible upon discontinuation of treatment [see Warnings and Precautions (5.2)].

Handling the Container

Instruct the patient to avoid allowing the tip of the dispensing container to contact the eye, surrounding structures, fingers, or any other surface in order to avoid contamination of the solution by common bacteria known to cause ocular infections. Serious damage to the eye and subsequent loss of vision may result from using contaminated solutions [see Warnings and Precautions (5.6)].

When to Seek Physician Advice

Advise the patient that if they develop an intercurrent ocular condition (e.g., trauma or infection), have ocular surgery, or develop any ocular reactions, particularly conjunctivitis and eyelid reactions, they should immediately seek their physician's advice concerning the continued use of TRAVATAN Z [see Warnings and Precautions (5.3, 5.4, 5.5)].

Use with Contact Lenses

Contact lenses should be removed prior to instillation of TRAVATAN Z and may be reinserted 15 minutes following its administration [see Warnings and Precautions (5.7)].

Use with Other Ophthalmic Drugs

If more than one topical ophthalmic drug is being used, the drugs should be administered at least 5 minutes between applications.

**TIMOPTIC is a registered trademark of Merck & Co., Inc.

Manufactured by

Novartis Manufacturing NV

Puurs-Sint-Amands, Belgium for

Sandoz Inc., Princeton, NJ 08540

9107971 US

PRINCIPAL DISPLAY PANEL

NDC 66758-095-75 Rx Only

TRAVATAN Z®

(travoprost ophthalmic

solution) 0.004%

FOR EYE USE ONLY

5 mL
STERILE

SANDOZ